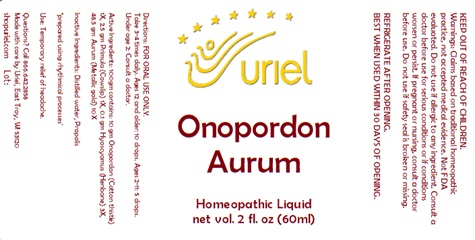 DRUG LABEL: Onopordon Aurum
NDC: 48951-7088 | Form: LIQUID
Manufacturer: Uriel Pharmacy Inc.
Category: homeopathic | Type: HUMAN OTC DRUG LABEL
Date: 20240221

ACTIVE INGREDIENTS: GOLD 10 [hp_X]/1 mL; ONOPORDUM ACANTHIUM FLOWER 1 [hp_X]/1 mL; PRIMULA VERIS FLOWER 1 [hp_X]/1 mL; HYOSCYAMUS NIGER LEAF 3 [hp_X]/1 mL
INACTIVE INGREDIENTS: WATER; PROPOLIS WAX

Onopordon Aurum

INDICATIONS AND USAGE

Directions: FOR ORAL USE ONLY.

DOSAGE AND ADMINISTRATION

Take 3-4 times daily. Ages 12 and older: 10 drops. Ages 2-11: 5 drops. Under age 2: Consult a doctor.

ACTIVE INGREDIENT

Active Ingredients: 100gm contains: 10 gm Onopordon (Cotton thistle) 1X, 2.5 gm Primula (Cowslip) 1X, 0.1 gm Hyoscyamus (Henbane) 3X, 48.5 gm Aurum (Metallic gold) 10X

Inactive Ingredients: Distilled water, Propolis

"prepared using rhythmical processes"

PURPOSE

Use: Promotes healthy circulatory support.

KEEP OUT OF REACH OF CHILDREN.

WARNINGS

Warnings: Claims based on traditional homeopathic practice, not accepted medical evidence. Not FDA evaluated. Do not use if allergic to any ingredient. Consult a doctor before use for serious conditions or if conditions worsen or persist. If pregnant or nursing, consult a doctor before use. Do not use if safety seal is broken or missing.

REFRIGERATE AFTER OPENING.
BEST WHEN USED WITHIN 30 DAYS OF OPENING.

QUESTIONS

Questions? Call 866.642.2858 Made with care by Uriel, East Troy, WI 53120 shopuriel.com Lot: